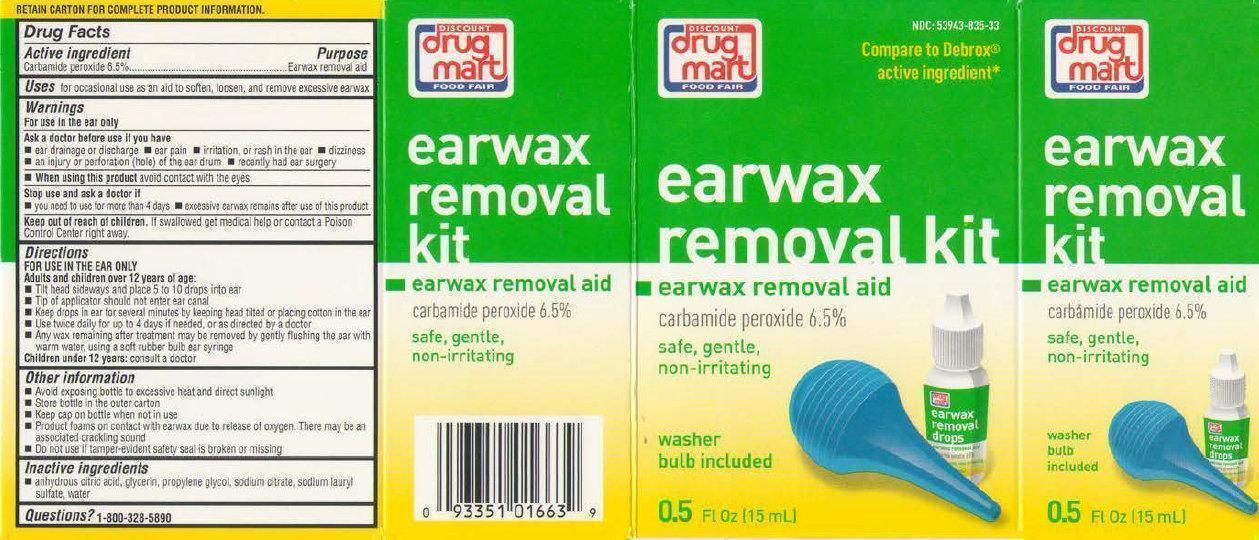 DRUG LABEL: DISCOUNT drug mart FOOD FAIR earwax removal kit
NDC: 53943-835 | Form: SOLUTION
Manufacturer: Discount Drug Mart
Category: otc | Type: HUMAN OTC DRUG LABEL
Date: 20231215

ACTIVE INGREDIENTS: CARBAMIDE PEROXIDE 65 mg/1 mL
INACTIVE INGREDIENTS: ANHYDROUS CITRIC ACID; GLYCERIN; PROPYLENE GLYCOL; SODIUM CITRATE; SODIUM LAURYL SULFATE; WATER

DISCOUNT drug mart FOOD FAIR earwax removal kit

Active ingredient

Carbamide peroxide 6.5%

Purpose

Earwax removal aid

Uses

for occasional use as an aid to soften, looser, and remove excessive earwax

Warnings

For use in the ear only

Ask a doctor before use if you have

- Ear drainage or discharge
- Ear pain
- Irritation, or rash in the ear
- Dizziness
- An injury or perforation (hole) of the ear drum
- Recently had ear surgery

When using this product

avoid contact with the eyes

Stop use and ask a doctor if

- You need to use for more than 4 days
- Excessive earwax remains after use of this product

Keep out of reach of children

If swallowed get medical help or contact a Poison Control Center right away.

Directions

FOR USE IN THE EAR ONLYAdults and children over 12 years of age:

Children under 12 years: consult a doctor

- Tilt head sideways and place 5 to 10 drops into ear
- Tip of applicator should not enter ear canal
- Keep drops in ear for several minutes by keeping head titled or placing cotton in the ear
- Use twice daily for up to 4 days if needed, or as directed by a doctor
- Any wax remaining after treatment may be removed by gently flushing the ear with warm water, using a soft rubber bulb ear syringe

Other Information

- Avoid exposing bottle to excessive heat and direct sunlight
- Store bottle in the outer carton
- Keep cap on bottle when not in use
- Product foams on contact with earwax due to release of oxygen. There many be an associated cracking sound
- Do not use if tamper-evident safety seal is broken or missing

Inactive ingredients

anhydrous citric acid, glycerin, propylene glycol, sodium citrate, sodium lauryl sulfate, water

Questions?

1-800-328-5890

*This product is not manufactured or distributed by Prestige Brands Inc. owner of the registered trademark Debrox.

If Dissatisfied, Return Unused Portion And Package To Store Where Purchased. If Unable To Return To Store, Send Reason For Dissatisfaction. Name, Address And Empty Package To: Discount Drug Mart, 211 Commerce Drive, Median Ohio 44256 Satisfaction Guaranteed

Distributed By: Drug Mart-Food Fair 211 Commerce Dr., Median, Ohio 44256 Made in the USA

PACKAGE LABEL

Discount Drug Mart Food Fair Earwax Removal Kit Earwax Removal Aid Carbamide Peroxide 6.5% Safe, Gentle, Non-Irritating Washer Bulb Included 0.5 FL OZ (15 mL)